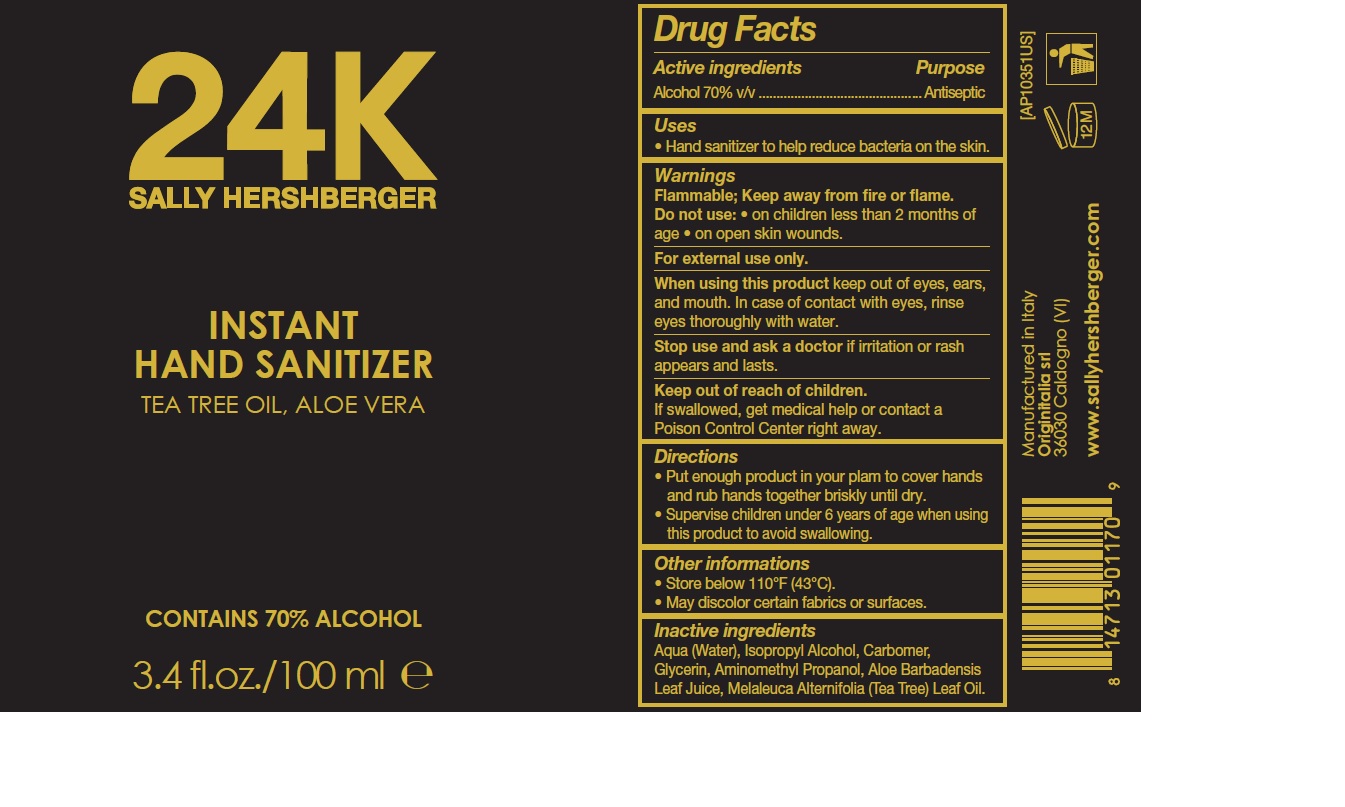 DRUG LABEL: 24K SALLY HERSHBERGER INSTANT HAND SANITIZER
NDC: 76607-001 | Form: GEL
Manufacturer: Sally Hershberger Professional Haircare, LLC
Category: otc | Type: HUMAN OTC DRUG LABEL
Date: 20200429

ACTIVE INGREDIENTS: ALCOHOL 70 mL/100 mL
INACTIVE INGREDIENTS: WATER; ISOPROPYL ALCOHOL; TEA TREE OIL; CARBOMER HOMOPOLYMER, UNSPECIFIED TYPE; ALOE VERA LEAF; AMINOMETHYLPROPANOL; GLYCERIN

24K SALLY HERSHBERGER INSTANT HAND SANITIZER

Active ingredients

Alcohol 70% v/v

Purpose

Antiseptic

Uses

- Hand sanitizer to help reduce bacteria on the skin

Warnings

Flammable; Keep away from fire or flame.

For external use only

Do not use

- on children less than 2 months of age
- on open skin wounds

When using this product

keep out of eyes, ears, and mouth. In case of contact with eyes, rinse eyes thoroughly with water.

Stop use and ask a doctor

if irritation or rash appears and lasts

Keep out of reach of children.

If swallowed, get medical help or contact a Poison Control Center right away.

Directions

- Put enough product in your palm to cover hands and rub hands together briskly until dry
- Supervise children under 6 years of age when using this product to avoid swallowing.

Other information

- Store below 110°F (43°C)
- May discolor certain fabrics or surfaces

Inactive ingredients

Aqua (Water), Isopropyl Alcohol, Carbomer, Glycerin, Aminomethyl Propanol, Aloe Barbadensis Leaf Juice, Melaleuca Alternifolia (Tea Tree) Leaf Oil.

Company Information

Manufactured in Italy

Originitalia srl

36030 Caldogno (VI)

www.sallyhershberger.com

Product Packaging - 100 ml bottle

24K

SALLY HERSHBERGER

INSTANT

HAND SANITIZER

TEA TREE OIL, ALOE VERA

CONTAINS 70% ALCOHOL

3.4 fl.oz./100 ml